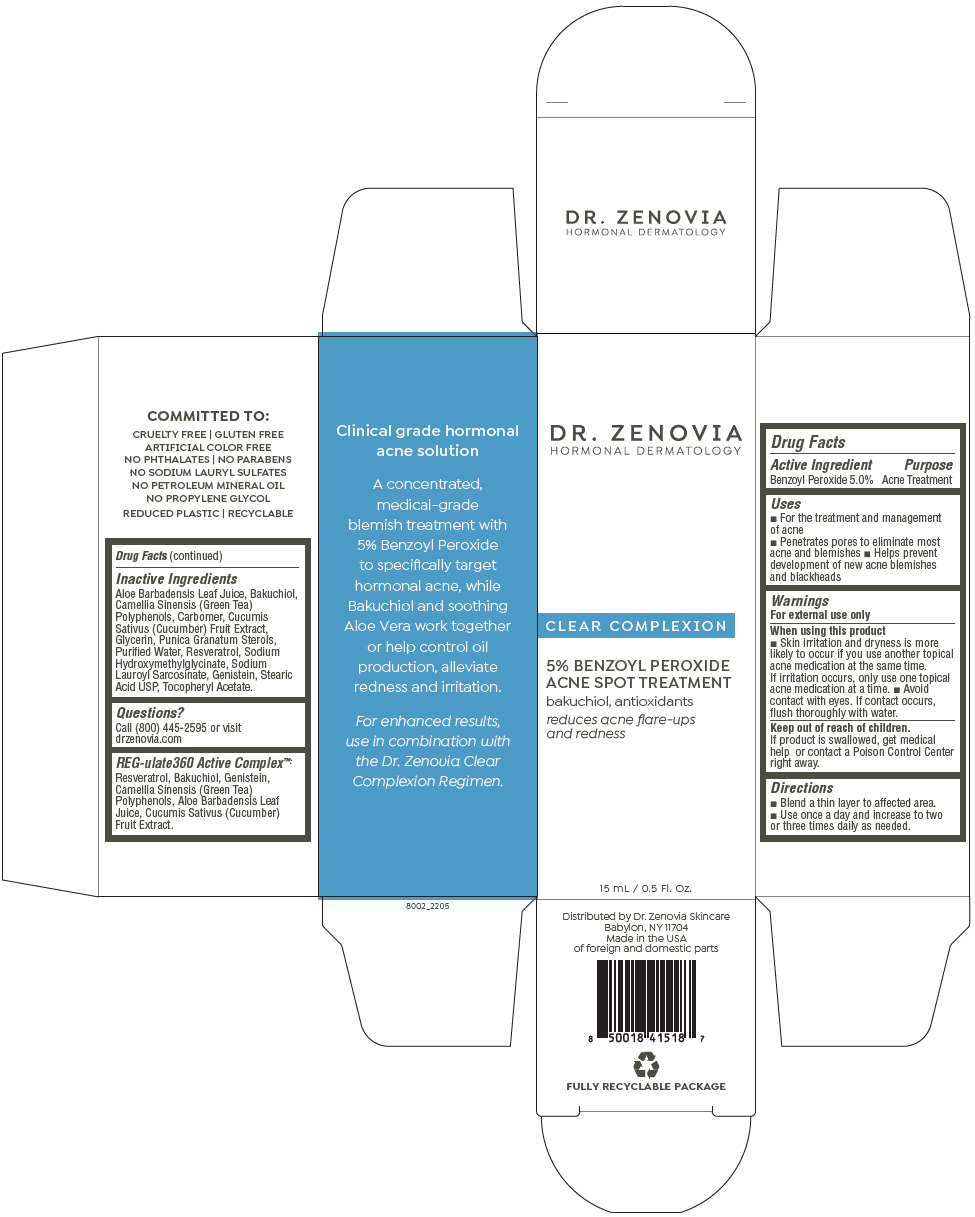 DRUG LABEL: Dr. Zenovia Spot Treatment
NDC: 51326-802 | Form: LIQUID
Manufacturer: Topiderm, Inc.
Category: otc | Type: HUMAN OTC DRUG LABEL
Date: 20240611

ACTIVE INGREDIENTS: BENZOYL PEROXIDE 50 mg/1 mL
INACTIVE INGREDIENTS: ALOE VERA LEAF; BAKUCHIOL; GREEN TEA LEAF; CARBOMER COPOLYMER TYPE A (ALLYL PENTAERYTHRITOL CROSSLINKED); CUCUMBER; GLYCERIN; PUNICA GRANATUM STEROLS; WATER; RESVERATROL; SODIUM HYDROXYMETHYLGLYCINATE; SODIUM LAUROYL SARCOSINATE; GENISTEIN; STEARIC ACID; .ALPHA.-TOCOPHEROL ACETATE, DL-

Dr. Zenovia Spot Treatment

Drug Facts

Active Ingredient

Benzoyl Peroxide 5.0%

Purpose

Acne Treatment

Uses

- For the treatment and management of acne
- Penetrates pores to eliminate most acne and blemishes
- Helps prevent development of new acne blemishes and blackheads

Warnings

For external use only

When using this product

- Skin irritation and dryness is more likely to occur if you use another topical acne medication at the same time. If irritation occurs, only use one topical acne medication at a time.
- Avoid contact with eyes. If contact occurs, flush thoroughly with water.

Keep out of reach of children.

If product is swallowed, get medical help or contact a Poison Control Center right away.

Directions

- Blend a thin layer to affected area.
- Use once a day and increase to two or three times daily as needed.

Inactive Ingredients

Aloe Barbadensis Leaf Juice, Bakuchiol, Camellia Sinensis (Green Tea) Polyphenols, Carbomer, Cucumis Sativus (Cucumber) Fruit Extract, Glycerin, Punica Granatum Sterols, Purified Water, Resveratrol, Sodium Hydroxymethylglycinate, Sodium Lauroyl Sarcosinate, Genistein, Stearic Acid USP, Tocopheryl Acetate.

Questions?

Call (800) 445-2595 or visit drzenovia.com

REG-ulate360 Active Complex™

Resveratrol, Bakuchiol, Genistein, Camellia Sinensis (Green Tea) Polyphenols, Aloe Barbadensis Leaf Juice, Cucumis Sativus (Cucumber) Fruit Extract.

Distributed by Dr. Zenovia Skincare
Babylon, NY 11704

PRINCIPAL DISPLAY PANEL - 15 mL Bottle Carton

DR. ZENOVIA
HORMONAL DERMATOLOGY

CLEAR COMPLEXION

5% BENZOYL PEROXIDE
ACNE SPOT TREATMENT

bakuchiol, antioxidants

reduces acne flare-ups
and redness

15 mL / 0.5 Fl. Oz.